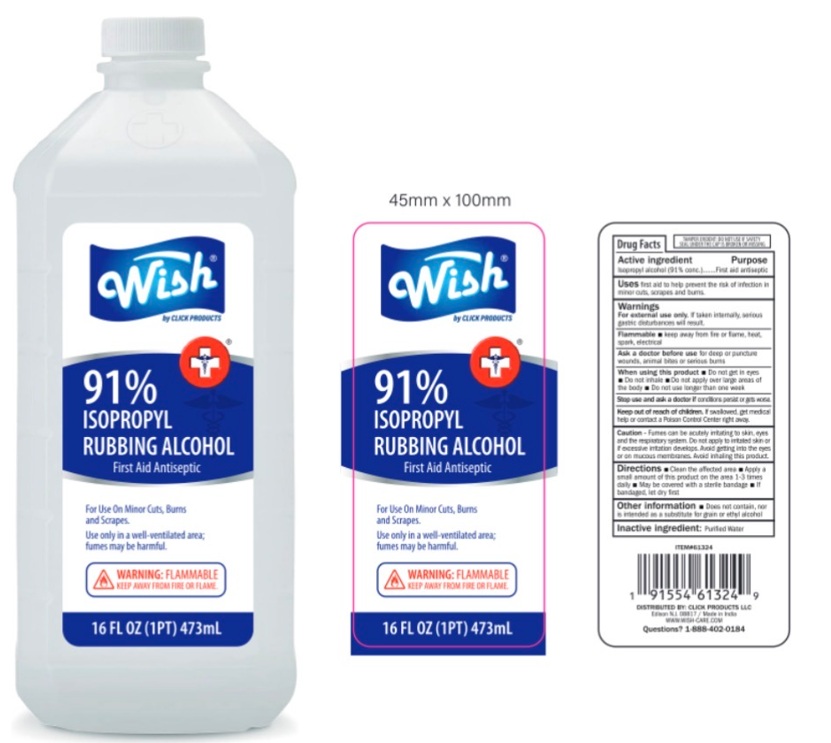 DRUG LABEL: WISH RUBBING ALCOHOL 91%
NDC: 84809-011 | Form: LIQUID
Manufacturer: LJ Pharma
Category: otc | Type: HUMAN OTC DRUG LABEL
Date: 20260130

ACTIVE INGREDIENTS: ISOPROPYL ALCOHOL 91 mL/100 mL
INACTIVE INGREDIENTS: WATER

Active Ingredient

Isopropyl Alcohol 91%

Purpose

FIRST AID ANTISEPTIC

Uses

First aid to help prevent the risk of infection in minor cuts, Scrapes & Burns.

Warnings

- For external use only. If taken internally, serious gastric disturbances will result.
- Flammable—keep away from fire, heat, sparks, electrical devices or use near open flame.
- Ask a doctor before useif you have deep or puncture wounds, animal bites or serious burns.
- When using this product

• Do not get in eyes.
• Do not apply over large areas of the body.
• Do not use longer than one week unless directed by a doctor.

Stop use and ask a doctor ifconditions persist or get worse.

Keep out of reach of children. In case of ingestion, get medical help or contact a Poison Control Center right away.

Caution: Fumes can be acutely irritating to skin, eyes and the respiratory system. Do not apply to irritated skin or excessive amounts. Avoid getting into the eyes or on mucous membranes. Avoid inhaling this product.

Directions

- Clean the affected Area
- Apply small amount of this product on the area 1-3 times daily
- Let the alcohol dry on skin before using bandages.
- May be covered with a sterile bandag.

Other information

- Store ate room temperature
- Does not contain, nor is intended as a substitute for grain or ethyl alchol.

Inactive Ingredients

Purified water